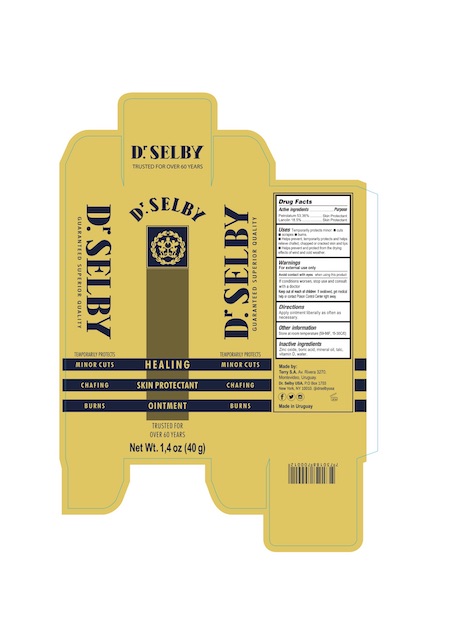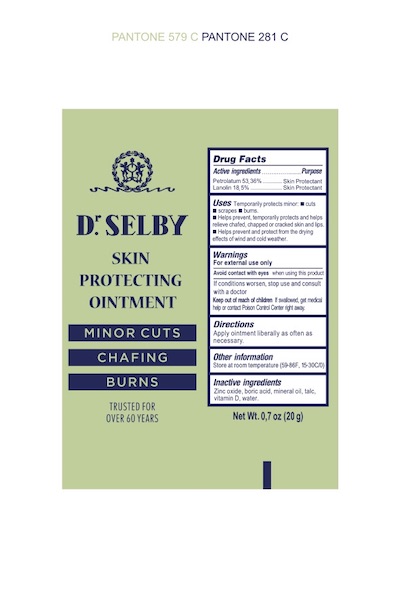 DRUG LABEL: Dr. Selby Crema Curativa
NDC: 47143-002 | Form: OINTMENT
Manufacturer: TERRY S.A.
Category: otc | Type: HUMAN OTC DRUG LABEL
Date: 20190318

ACTIVE INGREDIENTS: PETROLATUM 0.536 g/1 g; LANOLIN 0.185 g/1 g
INACTIVE INGREDIENTS: WATER; TALC; ZINC OXIDE; BORIC ACID; MINERAL OIL; VITAMIN D

Dr. Selby Crema Curativa 40g and 20g

Active ingredient Purpose
Lanolin 18.5% ..................................................Skin protectant
Petrolatum 53.36%.............................................Skin protectant

INDICATIONS AND USAGE

temporarily protects minor - cuts - scrapes - burns

helps prevent, temporarily protects and helps relieve chapped, chafed or cracked skin and lips

helps prevent and protect from the drying effects of wind and cold weather

Keep out of the reach of children.
If swallowed, get medical help or contact
a Poison Control Center right away.

WARNINGS

For external use only.

Avoid contact with eyes when using this product.

If conditions worsen, stop use and consult with a doctor.

DOSAGE AND ADMINISTRATION

Apply ointment liberally as often as needed.

INACTIVE INGREDIENT

Zinc oxide

Boric acid

Mineral Oil

Talc

Vitamin D

Water

PURPOSE

Skin Protectant